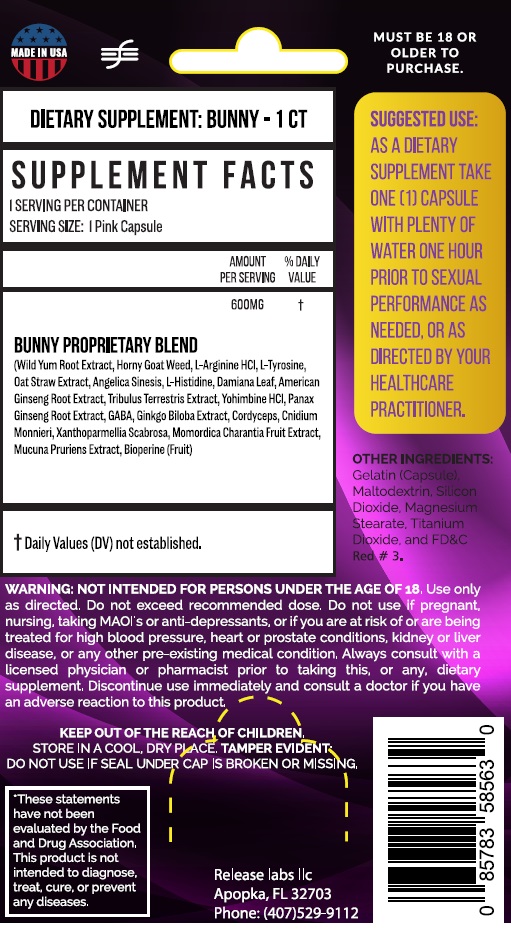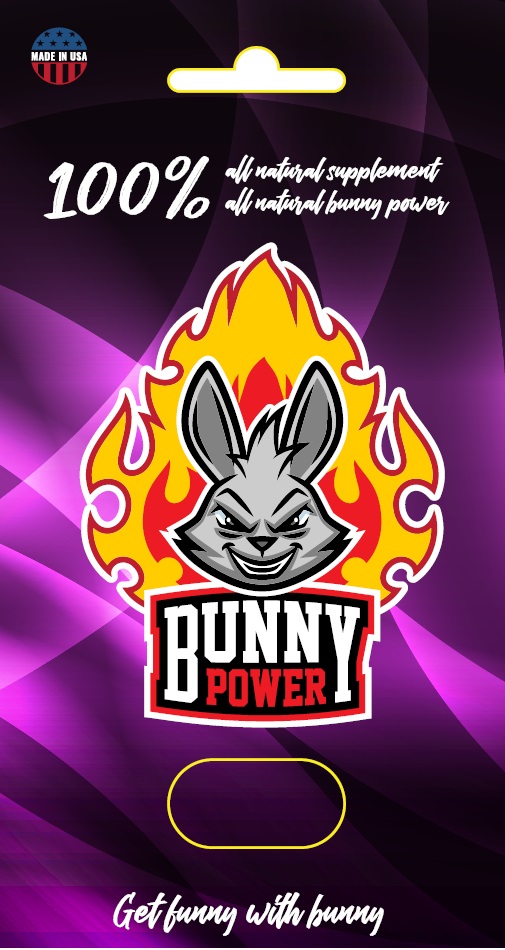 DRUG LABEL: BUNNY POWER
NDC: 71724-201 | Form: CAPSULE
Manufacturer: FLPHARMACEUTICALS LLC
Category: other | Type: DIETARY SUPPLEMENT
Date: 20190215

ACTIVE INGREDIENTS: DIOSCOREA VILLOSA ROOT 30 mg/1 1; EPIMEDIUM GRANDIFLORUM TOP 175 mg/1 1; ARGININE HYDROCHLORIDE 40 mg/1 1; TYROSINE 60 mg/1 1; AVENA SATIVA LEAF 5 mg/1 1; ANGELICA SINENSIS ROOT 2.5 mg/1 1; HISTIDINE 100 mg/1 1; TURNERA DIFFUSA LEAF 50 mg/1 1; AMERICAN GINSENG 40 mg/1 1; TRIBULUS TERRESTRIS ROOT 25 mg/1 1; PANAX GINSENG FRUIT 40 mg/1 1; GINKGO 40 mg/1 1; CORDYCEPS GUNNII FRUITING BODY 10 mg/1 1; CNIDIUM MONNIERI FRUIT 15 mg/1 1; MOMORDICA CHARANTIA FRUIT 50 mg/1 1; MUCUNA PRURIENS WHOLE 40 mg/1 1; BLACK PEPPER 25 mg/1 1
INACTIVE INGREDIENTS: MALTODEXTRIN; SILICON DIOXIDE; MAGNESIUM STEARATE; GELATIN; TITANIUM DIOXIDE; FD&C RED NO. 3

BUNNY POWER

STATEMENT OF IDENTITY

These statements have not been evaluated by the Food and Drug Administration.

HEALTH CLAIM

This product is not intended to diagnose, treat, cure, or prevent any disease.

WARNINGS

Use only as directed. Do not exceed recommended dosage.

Must be 18 or older to purchase.

Do not use if pregnant, nursing, taking MAOI's or anti-depressants, or if you are at risk of or are being treated for high blood pressure, heart or prostate conditions, kidney or liver disease, or any other pre-existing medical condition. Always consult with a licensed physician or pharmacist prior to taking this, or any, dietary supplement.

Discontinue use immediately and consult a doctor if you have an adverse reaction to this product.

SAFE HANDLING WARNING

Store at room temperature in a cool, dry place. Do not use if seal is broken or missing.

KEEP OUT OF REACH OF CHILDREN. NOT INTENDED FOR PERSONS UNDER THE AGE OF 18.

DOSAGE AND ADMINISTRATION

SUGGESTED USE: As a dietary supplement, take 1 capsule with plenty of water one hour prior to sexual performance as needed, or as directed by your Healthcare Practitioner.